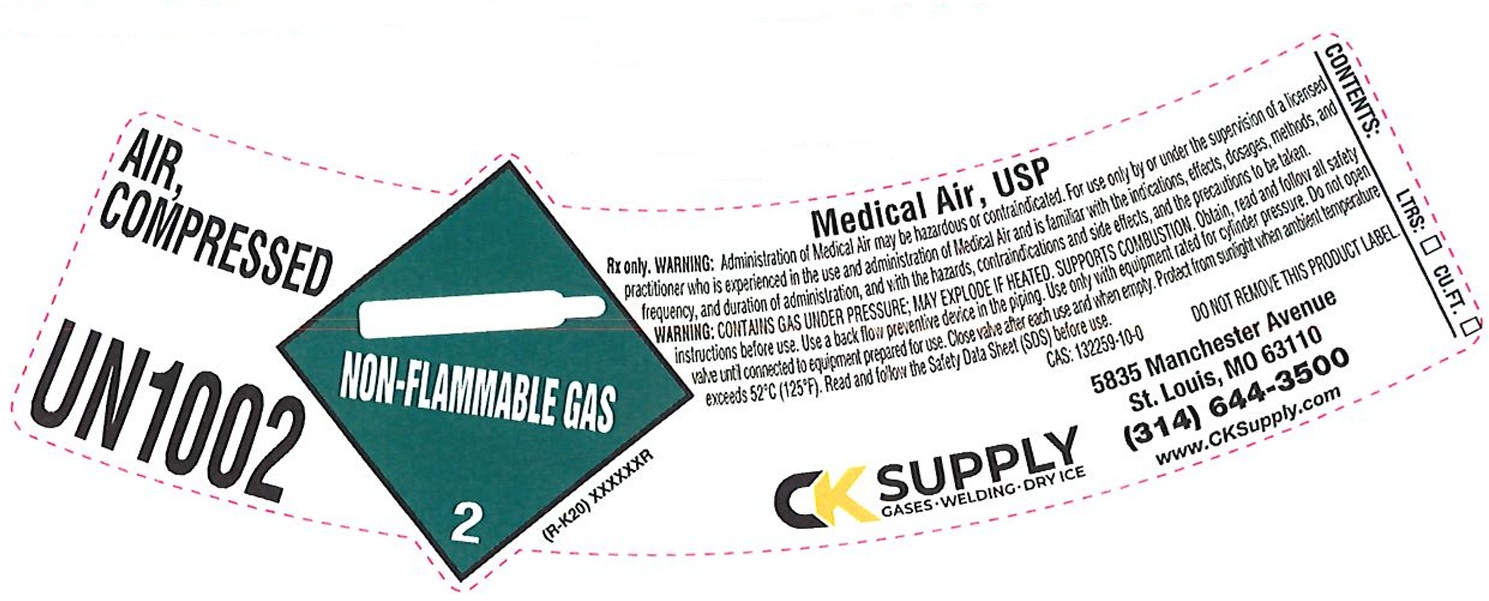 DRUG LABEL: Air
NDC: 10218-003 | Form: GAS
Manufacturer: Cee-Kay Supply, Inc.
Category: prescription | Type: HUMAN PRESCRIPTION DRUG LABEL
Date: 20251117

ACTIVE INGREDIENTS: AIR 100 L/100 L

air

PACKAGE LABEL

AIR, COMPRESSED

UN1002

Medical Air, USP

Rx only. WARNING: Administration of Medical Air may be hazardous or contraindicated. For use only by or under the supervision of a licensed practitioner who is experienced in the use and administration of Medical Air and is familiar with the indications, effects, dosages, methods, and frequency, and duration of administration, and with the hazards, contraindications and side effects, and the precautions to be taken.

WARNING: CONTAINS GAS UNDER PRESSURE; MAY EXPLODE IF HEATED. SUPPORTS COMBUSTION. Obtain, read and follow all safety instructions before use. Use a back flow preventive device in the piping. Use only with equipment rated for cylinder pressure. Do not open valve until connected to equipment prepared for use. Close valve after each use and when empty. Protect from sunlight when ambient temperature exceeds 52 C (125 F). Read and follow the Safety Data Sheet (SDS) before use.

CAS: 132259-10-0 DO NOT REMOVE THIS PRODUCT LABEL.

CK SUPPLY CASES WELDING DRY ICE

5835 Manchester Avenue

St. Louis, MO 63110

(314) 644-3500

www.CKSupply.com

CONTENTS: LTRS: CU.FT.